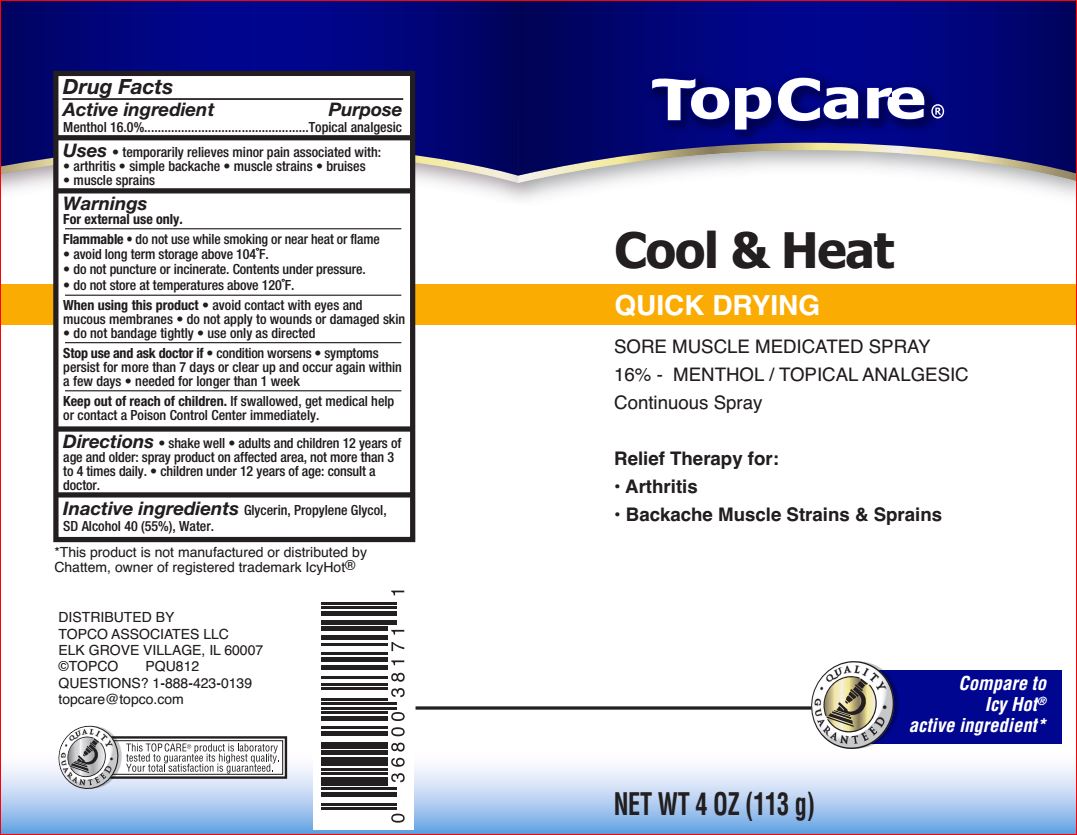 DRUG LABEL: Cool and Heat
NDC: 36800-730 | Form: SPRAY
Manufacturer: Top Care
Category: otc | Type: HUMAN OTC DRUG LABEL
Date: 20180718

ACTIVE INGREDIENTS: MENTHOL 16 g/100 g
INACTIVE INGREDIENTS: Glycerin; Propylene Glycol; Alcohol; Water

Drug Facts

Active ingredient Purpose

Menthol 16% Topical analgesic

Uses

• temporarily relief of pain and itching associated with:

• arthritis • simple backache • muscle strains • bruises • cramps • muscle sprains

Warnings For external use only

Flammable

• do not use while smoking or near heat or flame
• avoid long term storage above 104oF
• do not puncture or incinerate. Contents under pressure
• do not store at temperature above 120oF

When using this product

• avoid contact with eyes and mucous membranes
• do not apply to wounds or damages skin
• do not bandage tightly
• use only as directed

Stop use and ask a doctor if

• condition worsens
• symptoms last more than 7 days or clear up and occur again within a few days
•needed for longer than 1 week

KEEP OUT OF REACH OF CHILDREN

Keep out of reach of the children. If swallowed, get medical help or contact a Poison Control Center right away

If pregnant or breast-feeding, ask a health professional before use.

Directions

• shake well
• adults and children 12 years of age and older: spray on affected area, not more than 3 to 4 times daily
• children under 12 years of age: consult a doctor

Inactive ingredients

Glycerin, Propylene Glycol, SD Alcohol 40, Water